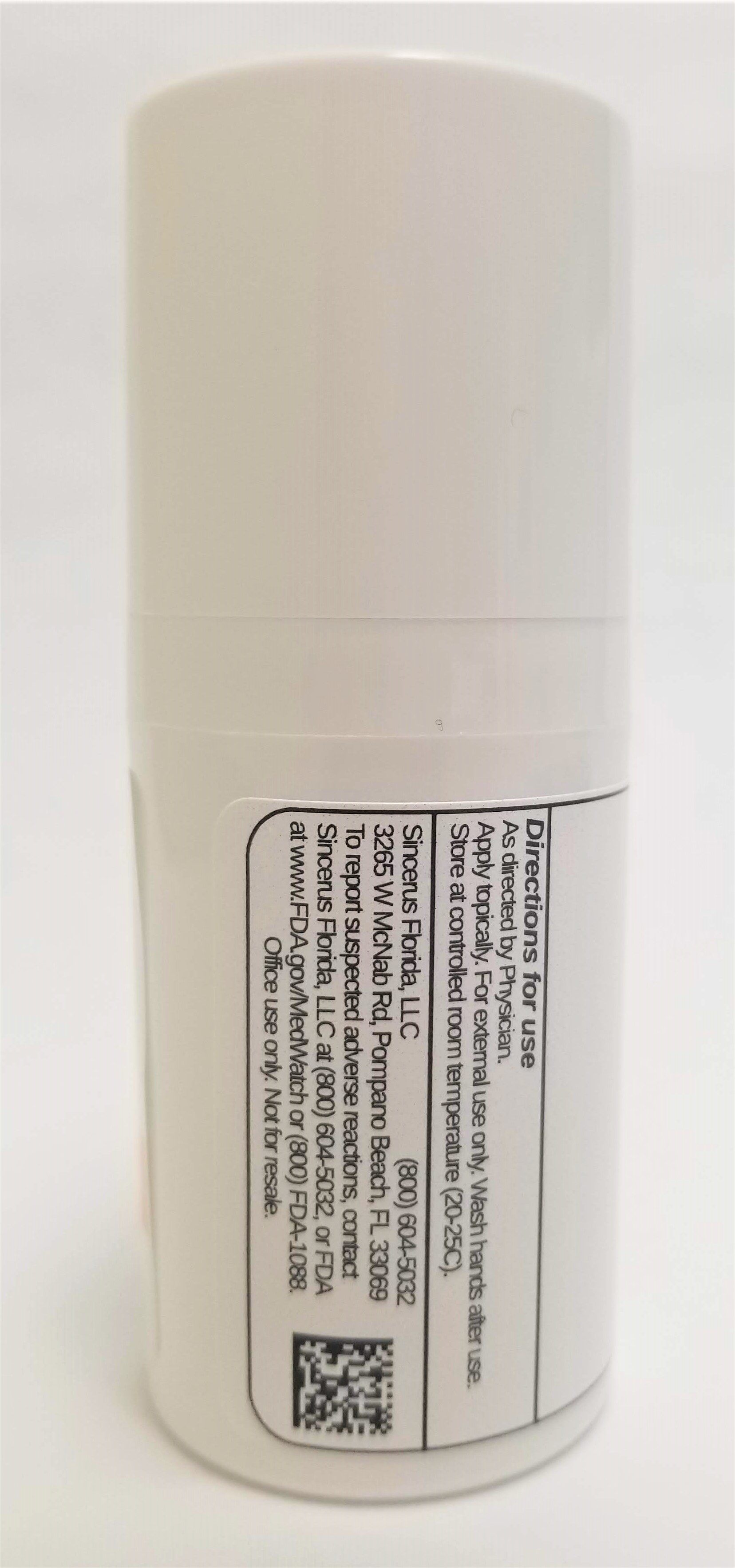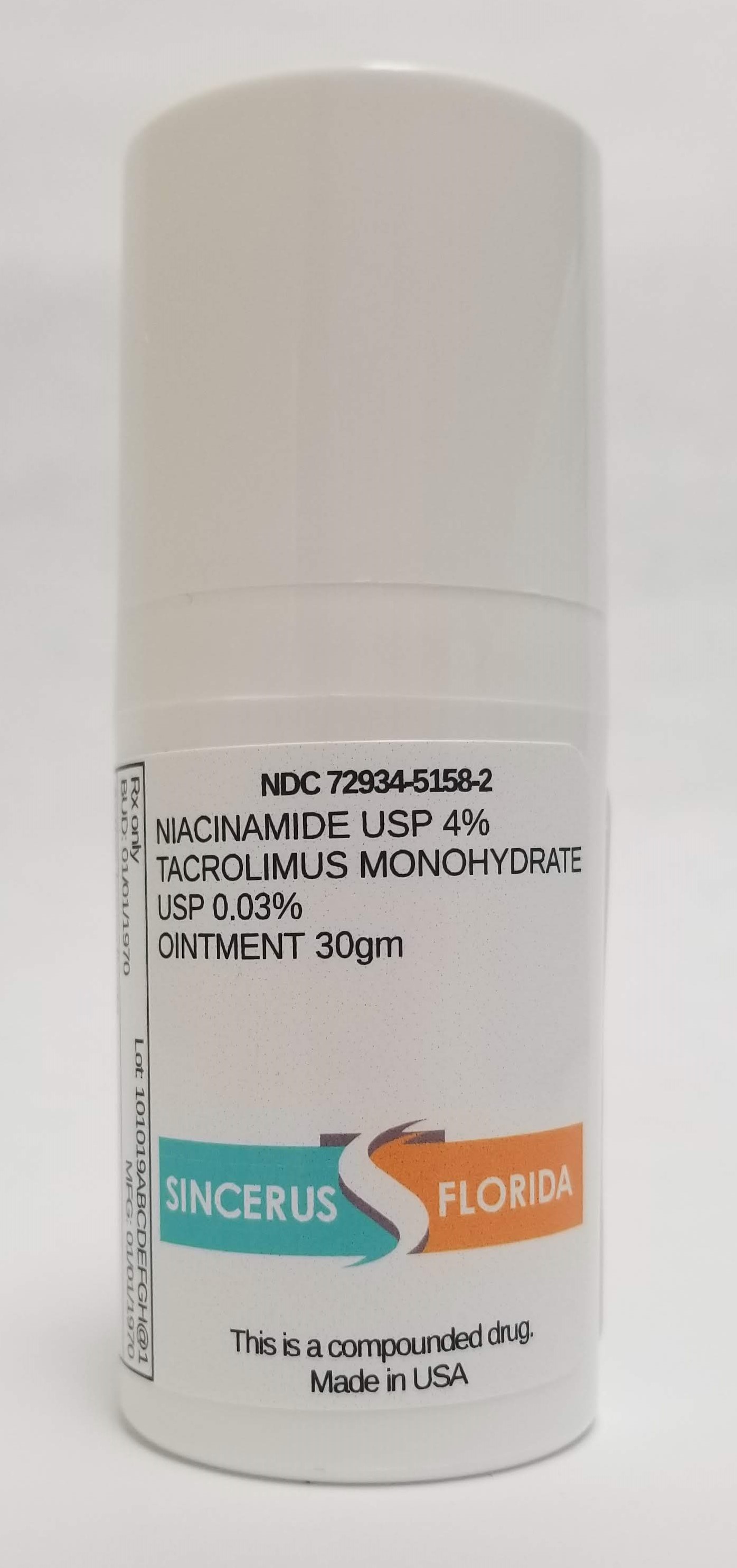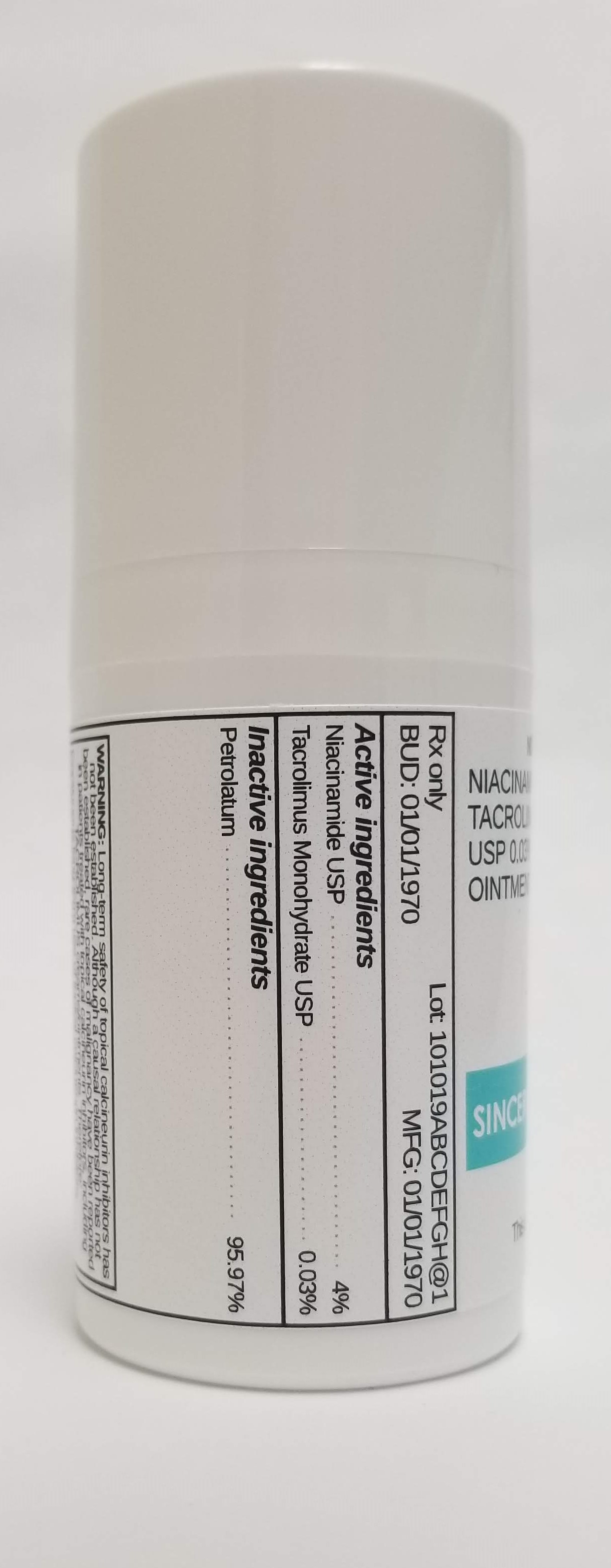 DRUG LABEL: NIACINAMIDE 4% / TACROLIMUS 0.03%
NDC: 72934-5158 | Form: OINTMENT
Manufacturer: Sincerus Florida, LLC
Category: prescription | Type: HUMAN PRESCRIPTION DRUG LABEL
Date: 20190516

ACTIVE INGREDIENTS: TACROLIMUS 0.03 g/100 g; NIACINAMIDE 4 g/100 g

NIACINAMIDE 4% / TACROLIMUS 0.03%